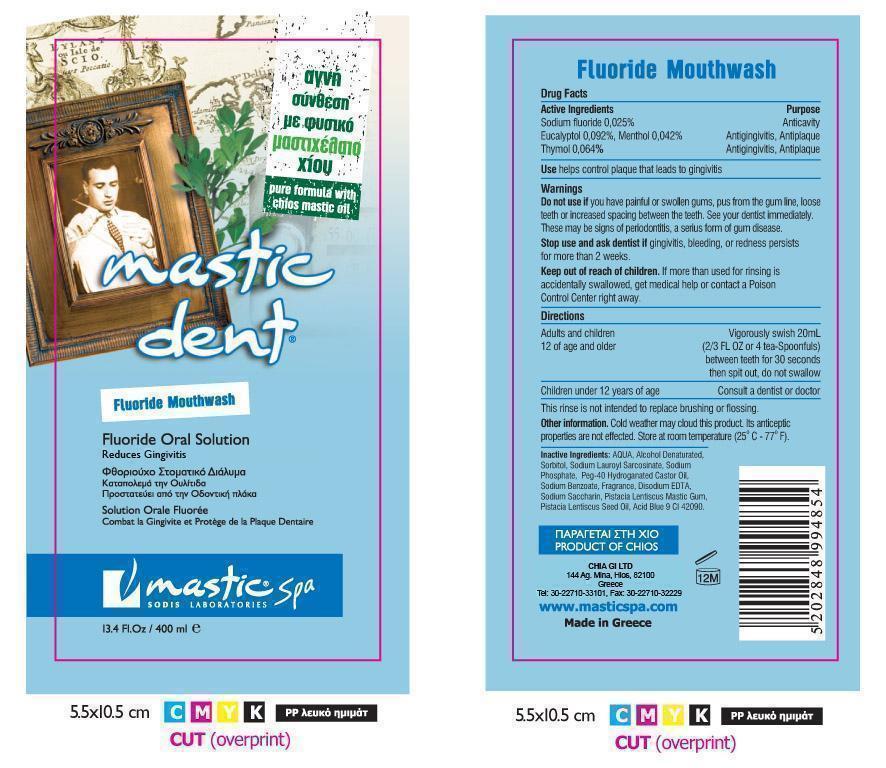 DRUG LABEL: Mastic Dent
NDC: 15304-4085 | Form: MOUTHWASH
Manufacturer: Chia Gi LTD
Category: otc | Type: HUMAN OTC DRUG LABEL
Date: 20121220

ACTIVE INGREDIENTS: SODIUM FLUORIDE 0.25 mg/1 mL; EUCALYPTOL 0.92 mg/1 mL; THYMOL 0.64 mg/1 mL; MENTHOL 0.42 mg/1 mL
INACTIVE INGREDIENTS: SORBITOL; PISTACIA LENTISCUS SEED OIL; PISTACIA LENTISCUS RESIN; SODIUM BENZOATE; ALCOHOL; SACCHARIN SODIUM; SODIUM LAUROYL SARCOSINATE; EDETATE DISODIUM; SODIUM PHOSPHATE; POLYOXYL 40 HYDROGENATED CASTOR OIL; FD&C BLUE NO. 1

Active Ingredients

Drug Facts:

Active Ingredients:

- Sodium Fluoride 0.025% - Anticavity
- Eucalyptol 0.092%, Menthol 0.042% - Antigingivitis , Antiplaque
- Thymol 0.064% - Antigingivitis, Antiplaque

Warnings

Warning:

- Do not use if you have painful or swollen gums, pus from the gum line, loose teeth or increased spacing between teeth. See your dentist immediately. These may be signs of periodontitis, a serious form of gum disease.
- Stop use and ask dentist if gingivitis, bleeding, or redness persists more than 2 weeks.

Keep out of reach of children. If more than used for rinsing is accidentally swallowed, get medical help or contact a Poison Control Center right away.

Directions

- Adults and children 12 of age and older - Vigorously swish 20mL (2.3 Fl. Oz or 4 tea-spoonfuls) between teeth for 30 seconds then spit out, do not swallow.
- Children under 12 years of age - Consult a dentist or doctor
- This rinse is not intended to replace brushing or flossing.

Other information

- Cold weather may cloud this product. Its anticeptic properties are not affected. Store at room temperature (25 C - 77 F).

Inactive Ingredients

AQUA, Alcohol Denaturated, Sorbitol, Sodium Lauroyl Sarcosinate, Sodium Phosphate, Peg-40 Hydrogenated Castor Oil, Sodium Benzoate, Fragrance, Disodium EDTA, Sodium Saccharin, Pistacia Lentiscus Mastic Gum, Pistacia Lentiscus Seed Oil, Acid Blue 9 CI 42090

Information of owner

Product Of Chios

CHIA GI LTD

144 AG. MINA, HIOS, 82100

GREECE
Tel.: 30-22710-33101, FAX: 30-22710-32229
www.masticspa.com
Made In Greece

PURPOSE SECTION

Reduces Gingivitis

Dosage

Dosage - Vigorously swish 20mL (2/3 Fl. OZ or 4 team - spoonfuls) between teeth for 30 seconds, then spit out do not swallow.